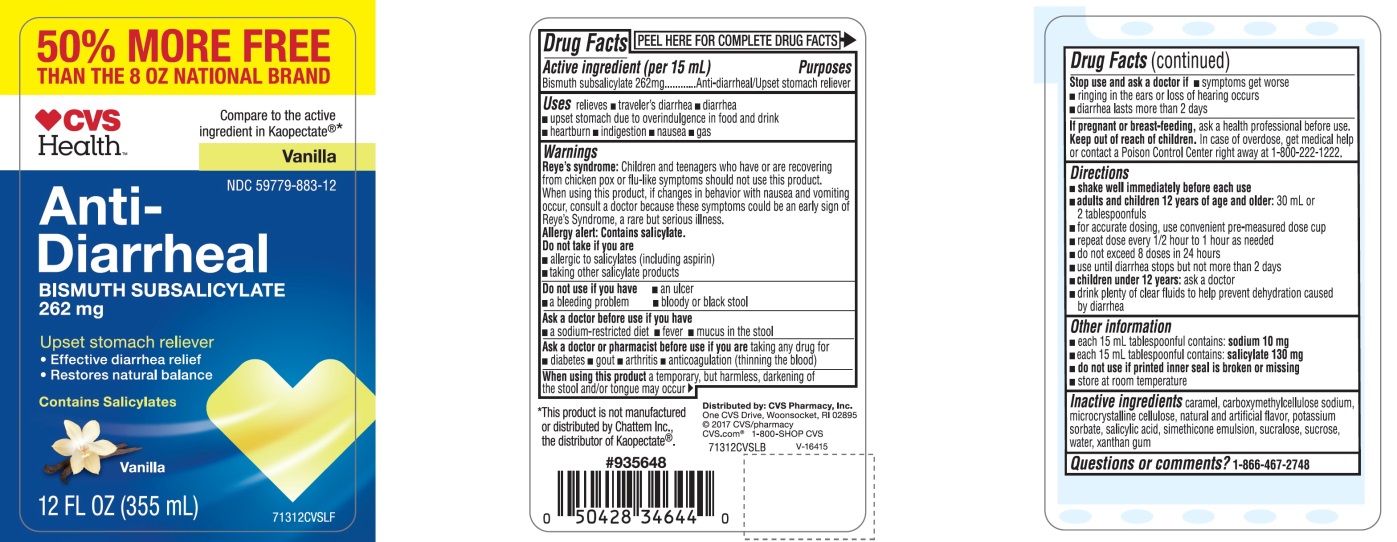 DRUG LABEL: CVS Health Anti-Diarrheal Vanilla
NDC: 59779-883 | Form: SUSPENSION
Manufacturer: CVS Pharmacy,Inc.
Category: otc | Type: HUMAN OTC DRUG LABEL
Date: 20251209

ACTIVE INGREDIENTS: BISMUTH SUBSALICYLATE 262 mg/15 mL
INACTIVE INGREDIENTS: CARAMEL; CARBOXYMETHYLCELLULOSE SODIUM, UNSPECIFIED; MICROCRYSTALLINE CELLULOSE; POTASSIUM SORBATE; SALICYLIC ACID; DIMETHICONE, UNSPECIFIED; SUCRALOSE; SUCROSE; WATER; XANTHAN GUM

CVS Health Anti-Diarrheal

Drug Facts

Active Ingredient (in each 15 ml)

Bismuth Subsalicylate 262 mg

Purposes

Antidiarrheal/Upset stomach reliever

Uses

relieves

- traveler’s diarrhea
- diarrhea
- upset stomach due to overindulgence in food and drink
- heartburn
- indigestion
- nausea
- gas

Warnings

Reye's syndrome:

Children and teenagers who have or are recovering from chicken pox or flu-like symptoms should not use this product. When using this product, if changes in behavior with nausea and vomiting occur, consult a doctor because these symptoms could be an early sign of Reye's syndrome, a rare but serious illness.

Allergy alert: Contains salicylate. Do not take if you are

- allergic to salicylates (including aspirin)
- taking other salicylate products

Do not use ifyou have

- an ulcer
- a bleeding problem
- bloody or black stool

Ask a doctor before use if you have

- a sodium-restricted diet
- fever
- mucus in the stool

Ask a doctor or pharmacist before use if you aretaking any drug for

- diabetes
- gout
- arthritis
- anticoagulation (thinning the blood)

WHEN USING

When using this producta temporary, but harmless, darkening of the stool and/or tongue may occur

Stop use and ask a doctor if

- symptoms get worse
- ringing in the ears or loss of hearing occurs
- diarrhea lasts more than 2 days

PREGNANCY OR BREAST FEEDING

If pregnant or breast-feeding,ask a health professional before use.

Keep out of reach of children.In case of overdose, get medical help or contact a Poison Control Center right away at 1-800-222-1222.

Directions

- shake well immediately before each use
- adults and children 12 years of age and older:30 ml or 2 tablespoonful
- for accurate dosing, use convenient pre-measured dose cup
- repeat dose every 1/2 hour to 1 hour as needed
- do not exceed 8 doses in 24 hours
- use until diarrhea stops but not more than 2 days
- children under 12 years:ask a doctor
- drink plenty of clear fluids to help prevent dehydration caused by diarrhea

Other information

- each 15mL tablespoon contains: sodium 10 mg
  - each 15mL tablespoon contains: salicylate 130 mg
  - do not use if printed inner seal is broken or missing
  - store at room temperature

Inactive ingredients

caramel, carboxymethylcellulose sodium, microcrystalline cellulose, natural and artificial flavor, potassium sorbate, salicylic acid , simethicone emulsion, sucralose, sucrose, water, xanthan gum

Questions or comments?

1-866-467-2748

PRINCIPAL DISPLAY PANEL - 355 mL Bottle Label

50% MORE FREE THAN THE 8 OZ NATIONAL BRAND

CVS Health™

NDC 59779-883-12

Compare to the active ingredient in Kaopectate®*

Vanilla

Anti-Diarrheal

Bismuth Subsalicylate, 262 mg

Upset stomach reliever

- Effective diarrhea relief
- Restores natural balance
- Contains Salicylates
- Vanilla

12 FL OZ (355 mL)

Distributed by: CVS Pharmacy, Inc.

One CVS Drive, Woonsocket, RI 02895

© 2017CVS/pharmacy

CVS.com®1-800-SHOP CVS

V-16415

*This product is not manufactured or distributed by Chattem Inc., the distributor of Kaopectate ®.